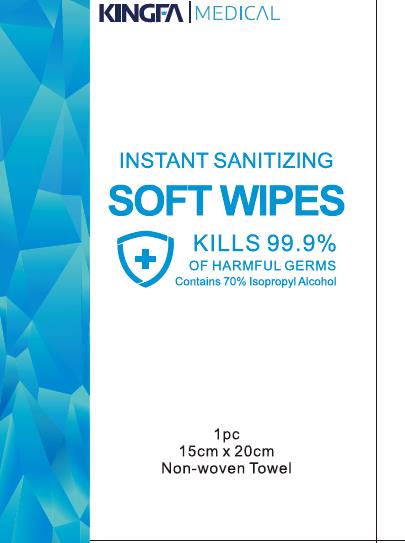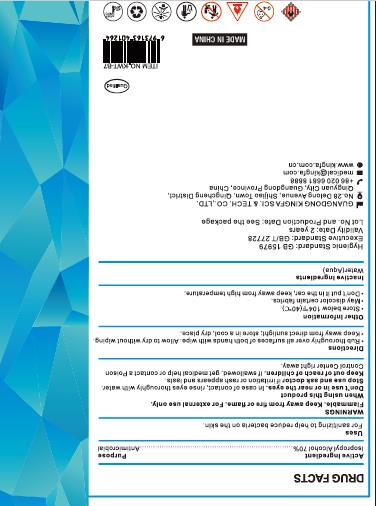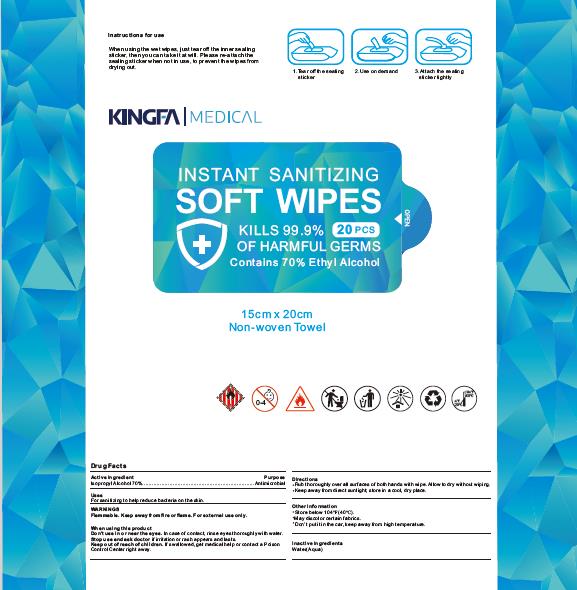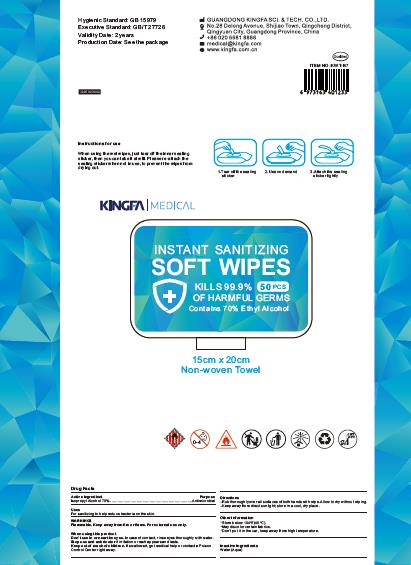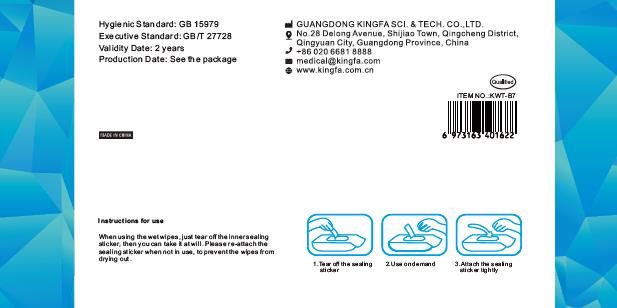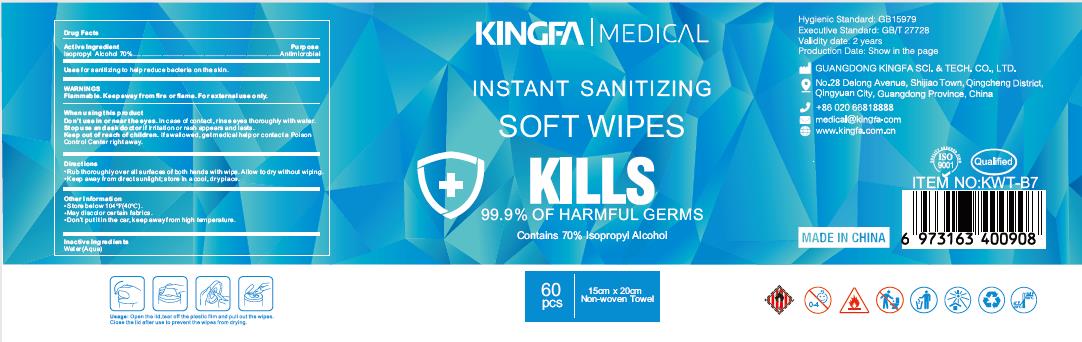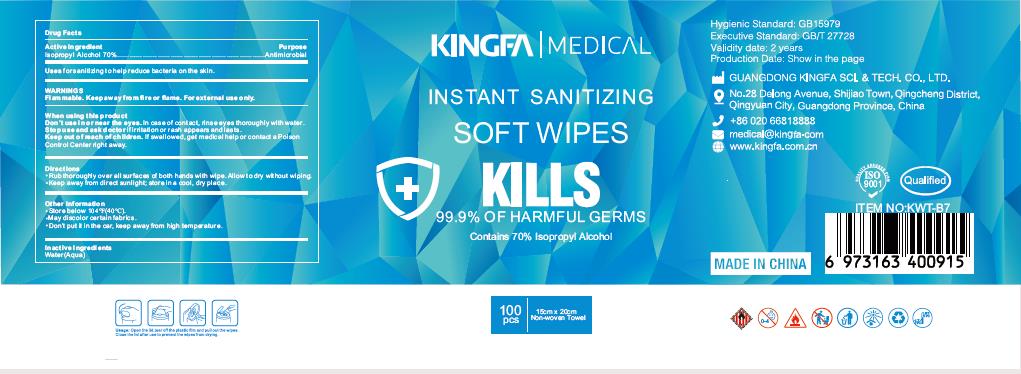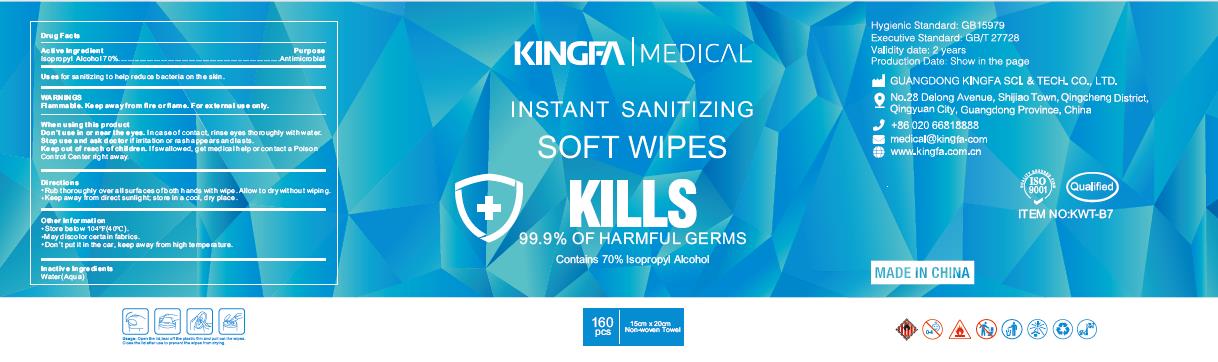 DRUG LABEL: Instant Sanitizing Soft Wipes
NDC: 80974-002 | Form: SWAB
Manufacturer: GUANGDONG KINGFA SCI.&TECH.CO.,LTD.
Category: otc | Type: HUMAN OTC DRUG LABEL
Date: 20201224

ACTIVE INGREDIENTS: ISOPROPYL ALCOHOL 70 g/100 g
INACTIVE INGREDIENTS: WATER

70 isopropyl alcohol jinfa

Active Ingredient(s)

isopropyl alcohol 70% v/v.

Purpose

Purpose: Antimicrobial

Uses

For sanitizing to help reduce bacteria on the skin.

Warnings

Flammable.Keep away from fire or flame. For external use only.

When using this product, avoid contact with eyes.

Do not use

in or near the eyes. In case of contact, rinse eyes thoroughly with water.

Stop use and ask a doctor if irritation or rash appears and lasts.

Keep out of reach of children. If swallowed, get medical help or contact a Poison Control Center right away.

Directions

- Rub thoroughly over all surfaces of both hands with wipe. Allow to dry without wiping.
- Keep away from dirct sunlight; store in a cool, dry place.

Other information

- Store below 104F(40C)
- May discolor certain fabrics.
- Don't put it in the car, keep away from high temperature.

Inactive ingredients

Water(Aqua)

Package Label - Principal Display Panel

20 PCS NDC 80974-002-01

50PCS NDC 80974-002-02

80PCS NDC 80974-002-03

1 PCS NDC 80974-002-07

60PCS NDC 80974-002-04

100PCS NDC 80974-002-05

160PCS NDC 80974-002-06